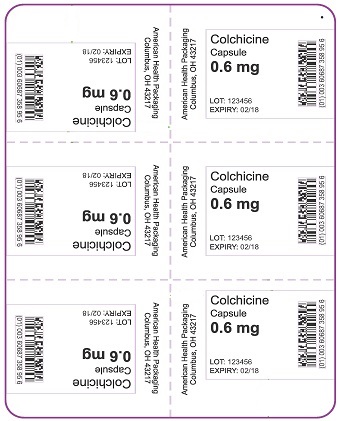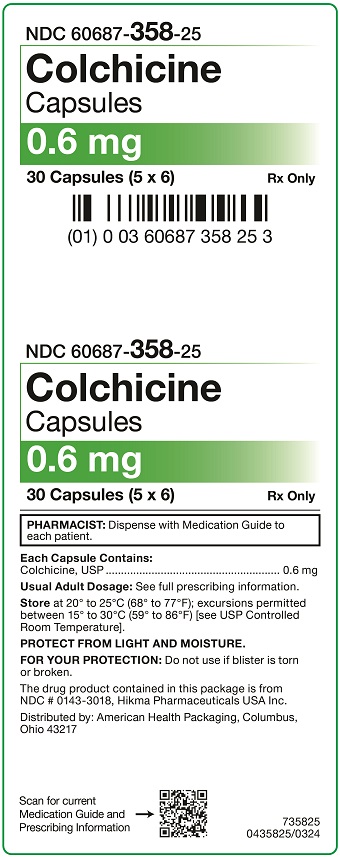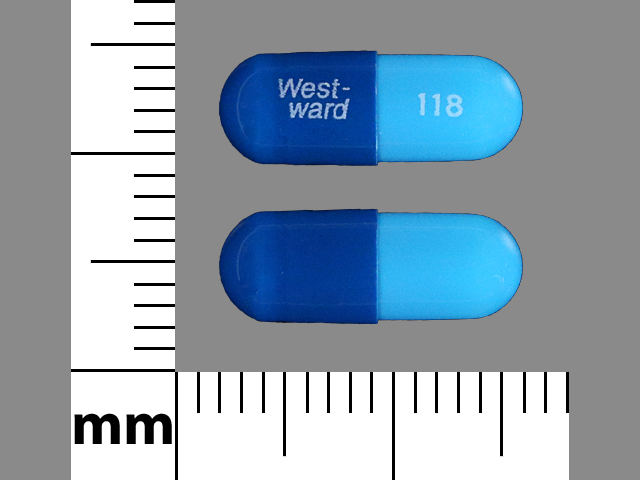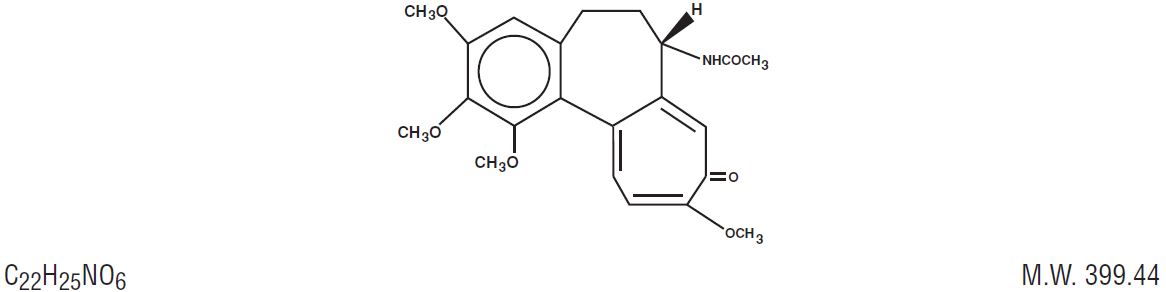 DRUG LABEL: Colchicine
NDC: 60687-358 | Form: CAPSULE
Manufacturer: American Health Packaging
Category: prescription | Type: HUMAN PRESCRIPTION DRUG LABEL
Date: 20250515

ACTIVE INGREDIENTS: COLCHICINE 0.6 mg/1 1
INACTIVE INGREDIENTS: SILICON DIOXIDE; ANHYDROUS LACTOSE; MAGNESIUM STEARATE; MICROCRYSTALLINE CELLULOSE; SODIUM STARCH GLYCOLATE TYPE A POTATO; GELATIN, UNSPECIFIED; WATER; TITANIUM DIOXIDE; FD&C RED NO. 3; FD&C BLUE NO. 1

HIGHLIGHTS OF PRESCRIBING INFORMATION

These highlights do not include all the information needed to use COLCHICINE CAPSULES safely and effectively.
See full prescribing information for COLCHICINE CAPSULES.
COLCHICINE capsules, for oral use
Initial U.S. Approval: 1961

1 INDICATIONS AND USAGE

- Colchicine capsules are an alkaloid indicated for prophylaxis of gout flares in adults (1).

Limitations of Use:

- The safety and effectiveness of colchicine capsules for acute treatment of gout flares during prophylaxis has not been studied.
- Colchicine capsules are not an analgesic medication and should not be used to treat pain from other causes

2 DOSAGE AND ADMINISTRATION

- The recommended dosage is 0.6 mg (one capsule) once or twice daily (2). Maximum dose 1.2 mg/day.
- Colchicine capsules are administered orally, without regard to meals (2).

3 DOSAGE FORMS AND STRENGTHS

- 0.6 mg capsules (3).

4 CONTRAINDICATIONS

- Patients with renal or hepatic impairment should not be given colchicine capsules in conjunction with drugs that inhibit both P-gp and CYP3A4 (4).
- Patients with both renal and hepatic impairment should not be given colchicine capsules (4).

5 WARNINGS AND PRECAUTIONS

- Fatal overdoseshave been reported with colchicine in adults and children. Keep colchicine capsules out of the reach of children (5.1, 10).
- Blood dyscrasias: Myelosuppression, leukopenia, granulocytopenia, thrombocytopenia, and aplastic anemia have been reported (5.2).
- Monitor for toxicity and if present consider temporary interruption or discontinuation of colchicine (5.2, 5.3, 5.4, 6, 10).
- Drug interaction with dual P-gp and CYP3A4 inhibitors: Co-administration of colchicine with dual P-gp and CYP3A4 inhibitors has resulted in life-threatening interactions and death (5.3, 7).
- Neuromuscular toxicity: Myotoxicity including rhabdomyolysis may occur, especially in combination with other drugs known to cause this effect. Consider temporary interruption or discontinuation of colchicine capsules (5.4, 7).

6 ADVERSE REACTIONS

The most commonly reported adverse reactions with colchicine are gastrointestinal symptoms, including diarrhea, nausea, vomiting, and abdominal pain (6).

To report SUSPECTED ADVERSE REACTIONS, contact Hikma Pharmaceuticals USA Inc. at 1-800-962-8364 or FDA at 1-800-FDA-1088 or www.fda.gov/medwatch.

7 DRUG INTERACTIONS

- Co-administration of P-gp or CYP3A4 inhibitors or inhibitors of both P-gp and CYP3A4 (e.g., clarithromycin or cyclosporine) have been reported to lead to colchicine toxicity. The potential for drug-drug interactions must be considered prior to and during therapy.
- Concomitant use of colchicine capsules and inhibitors of CYP3A4 or P-gp should be avoided if possible. If co-administration of colchicine capsules and an inhibitor of CYP3A4 or P-gp is necessary, the dose of colchicine capsules should be reduced and the patient should be monitored carefully for colchicine toxicity (7, 12.3).

8 USE IN SPECIFIC POPULATIONS

- In the presence of renal or hepatic impairment, patients should be monitored closely and dose adjustment should be considered as necessary (8.6, 8.7).
- Pregnancy: Use only if the potential benefit justifies the potential risk to the fetus (8.1).
- Lactation: Caution should be exercised when administered to a breastfeeding woman (8.2).
- Females and Males of Reproductive Potential: Advise males that colchicine capsules may rarely and transiently impair fertility (8.3)
- Geriatric Use: The recommended dosage of colchicine should be based on renal/hepatic function (8.5).

FULL PRESCRIBING INFORMATION

1 INDICATIONS AND USAGE

Colchicine capsules are indicated for prophylaxis of gout flares in adults.

Limitations of Use: The safety and effectiveness of colchicine capsules for acute treatment of gout flares during prophylaxis has not been studied.

Colchicine capsules are not an analgesic medication and should not be used to treat pain from other causes.

2 DOSAGE AND ADMINISTRATION

2.1 Recommended Dosage for Gout Prophylaxis

For prophylaxis of gout flares, the recommended dosage of colchicine capsules is 0.6 mg once or twice daily. The maximum dosage is 1.2 mg per day.

Colchicine capsules are administered orally, without regard to meals.

3 DOSAGE FORMS AND STRENGTHS

0.6 mg capsules – No. 4 Dark Blue/Light Blue Hard Gelatin Capsules printed “West-ward 118” in white ink.

4 CONTRAINDICATIONS

Patients with renal or hepatic impairment should not be given colchicine capsules with drugs that inhibit both P-glycoprotein and CYP3A4 inhibitors [see Drug Interactions (7)]. Combining these dual inhibitors with colchicine in patients with renal or hepatic impairment has resulted in life-threatening or fatal colchicine toxicity.

Patients with both renal and hepatic impairment should not be given colchicine capsules.

5 WARNINGS AND PRECAUTIONS

5.1 Fatal Overdose

Fatal overdoses, both accidental and intentional, have been reported in adults and children who have ingested colchicine [see Overdosage (10)]. Colchicine capsules should be kept out of the reach of children.

5.2 Blood Dyscrasias

Myelosuppression, leukopenia, granulocytopenia, thrombocytopenia, pancytopenia, and aplastic anemia have been reported with colchicine used in therapeutic doses.

5.3 Interactions with CYP3A4 and P-gp Inhibitors

Because colchicine is a substrate for both the CYP3A4 metabolizing enzyme and the P-glycoprotein efflux transporter, inhibition of either of these pathways may lead to colchicine-related toxicity. Inhibition of both CYP3A4 and P-gp by dual inhibitors such as clarithromycin has been reported to produce life-threatening or fatal colchicine toxicity due to significant increases in systemic colchicine levels. Therefore, concomitant use of colchicine capsules and inhibitors of CYP3A4 or P-glycoprotein should be avoided [see Drug Interactions (7)]. If avoidance is not possible, reduced daily dose should be considered and the patient should be monitored closely for colchicine toxicity. Use of colchicine capsules in conjunction with drugs that inhibit both P-gp and CYP3A4 is contraindicated in patients with renal or hepatic impairment [see Contraindications (4)].

5.4 Neuromuscular Toxicity

Neuromuscular toxicity and rhabdomyolysis have been reported from chronic treatment with colchicine in therapeutic doses, especially in combination with other drugs known to cause this effect. Patients with impaired renal function and elderly patients (even those with normal renal and hepatic function) are at increased risk. Once colchicine treatment is ceased, the symptoms generally resolve within 1 week to several months.

6 ADVERSE REACTIONS

Gastrointestinal disorders are the most common adverse reactions with colchicine. They are often the first signs of toxicity and may indicate that the colchicine dosage needs to be reduced or therapy stopped. These include diarrhea, nausea, vomiting, and abdominal pain.

Colchicine has been reported to cause neuromuscular toxicity, which may present as muscle pain or weakness [see Warnings and Precautions (5.4)].

Toxic manifestations associated with colchicine include myelosuppression, disseminated intravascular coagulation, and injury to cells in the renal, hepatic, circulatory, and central nervous system. These most often occur with excessive accumulation or overdosage [see Overdosage (10)].

The following reactions have been reported with colchicine. These have been generally reversible by interrupting treatment or lowering the dose of colchicine:

Digestive: abdominal cramping, abdominal pain, diarrhea, lactose intolerance, nausea, vomiting

Neurological: sensory motor neuropathy

Dermatological: alopecia, maculopapular rash, purpura, rash

Hematological: leukopenia, granulocytopenia, thrombocytopenia, pancytopenia, aplastic anemia

Hepatobiliary: elevated AST, elevated ALT

Musculoskeletal: myopathy, elevated CPK, myotonia, muscle weakness, muscle pain, rhabdomyolysis

Reproductive: azoospermia, oligospermia

7 DRUG INTERACTIONS

Colchicine is a substrate of the efflux transporter P-glycoprotein (P-gp), and the CYP3A4 metabolizing enzyme. Fatal drug interactions have been reported when colchicine is administered with clarithromycin, a dual inhibitor of CYP3A4 and P-glycoprotein. Toxicities have also been reported when colchicine is administered with inhibitors of CYP3A4 that may not be potent inhibitors of P-gp (e.g., grapefruit juice, erythromycin, verapamil), or inhibitors of P-gp that may not be potent inhibitors of CYP3A4 (e.g., cyclosporine).

Patients with renal or hepatic impairment should not be given colchicine capsules with drugs that inhibit both P-glycoprotein and CYP3A4 [see Contraindications (4)]. Combining these dual inhibitors with colchicine capsules in patients with renal and hepatic impairment has resulted in life-threatening or fatal colchicine toxicity.

Physicians should ensure that patients are suitable candidates for treatment with colchicine capsules and remain alert for signs and symptoms of toxic reactions associated with increased colchicine exposure due to drug interactions. Signs and symptoms of colchicine toxicity should be evaluated promptly and, if toxicity is suspected, colchicine capsules should be discontinued immediately.

7.1 CYP3A4

The concomitant use of colchicine capsules and CYP3A4 inhibitors (e.g., clarithromycin, ketoconazole, grapefruit juice, erythromycin, verapamil, etc.) should be avoided due to the potential for serious and life-threatening toxicity [see Warnings and Precautions (5.3) and Clinical Pharmacology (12)] .

If co-administration of colchicine capsules and a CYP3A4 inhibitor is necessary, the dose of colchicine capsules should be adjusted by either reducing the daily dose or reducing the dose frequency, and the patient should be monitored carefully for colchicine toxicity [see Clinical Pharmacology (12)].

7.2 P-glycoprotein

The concomitant use of colchicine capsules and inhibitors of P-glycoprotein (e.g. clarithromycin, ketoconazole, cyclosporine, etc.) should be avoided due to the potential for serious and life-threatening toxicity [see Warnings and Precautions (5.3) and Clinical Pharmacology (12)] .

If co-administration of colchicine capsules and a P-gp inhibitor is necessary, the dose of colchicine capsules should be adjusted by either reducing the daily dose or reducing the dose frequency, and the patient should be monitored carefully for colchicine toxicity [see Clinical Pharmacology (12)] .

7.3 HMG-CoA Reductase Inhibitors and Fibrates

Some drugs such as HMG-CoA reductase inhibitors and fibrates may increase the risk of myopathy when combined with colchicine capsules. Complaints of muscle pain or weakness could be an indication to check serum creatinine kinase levels for signs of myopathy.

7.4 Drug-Drug Interaction Studies

Four pharmacokinetic studies evaluated the effects of co-administration of voriconazole (200 mg BID), fluconazole (200 mg QD), cimetidine (800 mg BID), and propafenone (225 mg BID) on systemic levels of colchicine. Colchicine can be administered with these drugs at the tested doses without a need for dose adjustment. However, these results should not be extrapolated to other co-administered drugs [see Drug Interactions (7.1, 7.2) and Pharmacokinetics (12.3)].

8 USE IN SPECIFIC POPULATIONS

8.1 Pregnancy

Risk Summary: Available data from published literature on colchicine use in pregnancy over several decades have not identified any drug associated risks for major birth defects, miscarriage, or other adverse maternal or fetal outcomes (see Data). Colchicine crosses the human placenta. Although animal reproductive and developmental studies were not conducted with colchicine capsules, published animal reproduction and development studies indicate that colchicine causes embryofetal toxicity, teratogenicity, and altered postnatal development at exposures within or above the clinical therapeutic range.

The background risk of major birth defects and miscarriage for the indicated population is unknown. All pregnancies have a background risk of birth defect, loss or other adverse outcomes. In the U.S. general population, the estimated background risk of major birth defects and miscarriage in clinically recognized pregnancies is 2 to 4% and 15 to 20%, respectively.

Data: Human Data: Available data from published observational studies, case series, and case reports over several decades do not suggest an increased risk for major birth defects or miscarriage in pregnant women with rheumatic diseases (such as rheumatoid arthritis, Behcet’s disease, or Familial Mediterranean Fever (FMF)) treated with colchicine at therapeutic doses during pregnancy. Limitations of these data include the lack of randomization and inability to control for confounders such as underlying maternal disease and maternal use of concomitant medications.

8.2 Lactation

Risk Summary: Colchicine is present in human milk (see Data). Adverse events in breastfed infants have not been reported in the published literature after administration of colchicine to lactating women. There are no data on the effects of colchicine on milk production. The developmental and health benefits of breastfeeding should be considered along with the mother’s clinical need for colchicine capsules and any potential adverse effects on the breastfed child from colchicine or from the underlying maternal condition.

Data: Human data:Limited published data from case reports and a small lactation study demonstrate that colchicine is present in breastmilk. A systematic review of literature reported no adverse effects in 149 breastfed children. In a prospective observational cohort study, no gastrointestinal or other symptoms were reported in 38 colchicine-exposed breastfed infants.

8.3 Females and Males of Reproductive Potential

Infertility: Case reports and epidemiology studies in human male subjects on colchicine therapy indicated that infertility from colchicine is rare and may be reversible.

8.4 Pediatric Use

Gout is rare in pediatric patients; the safety and effectiveness of colchicine capsules in pediatric patients has not been evaluated in controlled studies.

8.5 Geriatric Use

Because of the increased incidence of decreased renal function in the elderly population, and the higher incidence of other co-morbid conditions in the elderly population requiring the use of other medications, reducing the dosage of colchicine when elderly patients are treated with colchicine should be carefully considered.

8.6 Renal Impairment

No dedicated pharmacokinetic study has been conducted using colchicine capsules in patients with varying degrees of renal impairment. Colchicine is known to be excreted in urine in humans and the presence of severe renal impairment has been associated with colchicine toxicity. Urinary clearance of colchicine and its metabolites may be decreased in patients with impaired renal function. Dose reduction or alternatives should be considered for the prophylaxis of gout flares in patients with severe renal impairment. Colchicine is not effectively removed by hemodialysis. Patients who are undergoing hemodialysis should be monitored carefully for colchicine toxicity.

8.7 Hepatic Impairment

No dedicated pharmacokinetic study using colchicine capsules has been conducted in patients with varying degrees of hepatic impairment. Colchicine is known to be metabolized in humans and the presence of severe hepatic impairment has been associated with colchicine toxicity. Hepatic clearance of colchicine may be significantly reduced and plasma half-life prolonged in patients with chronic hepatic impairment.

Dose reduction or alternatives should be considered for the prophylaxis of gout flares in patients with severe hepatic impairment.

9 DRUG ABUSE AND DEPENDENCE

Tolerance, abuse, or dependence from colchicine has not been reported.

10 OVERDOSAGE

The dose of colchicine that would induce significant toxicity for an individual is unknown. Fatalities have been reported in patients after ingesting a dose as low as 7 mg over a 4-day period, while other patients have reportedly survived after ingesting more than 60 mg. A review of 150 patients who overdosed on colchicine found that those who ingested less than 0.5 mg/kg survived and tended to have milder adverse reactions, such as gastrointestinal symptoms, whereas those who ingested from 0.5 to 0.8 mg/kg had more severe adverse reactions, including myelosuppression. There was 100% mortality among patients who ingested more than 0.8 mg/kg.

- The first stage of acute colchicine toxicity typically begins within 24 hours of ingestion and includes gastrointestinal symptoms such as abdominal pain, nausea, vomiting, diarrhea, and significant fluid loss, leading to volume depletion. Peripheral leukocytosis may also be seen.
- Life-threatening complications occur during the second stage, which occurs 24 to 72 hours after drug administration, attributed to multi-organ failure and its associated consequences. Death usually results from respiratory depression and cardiovascular collapse. If the patient survives, recovery of multi-organ injury may be accompanied by rebound leukocytosis and alopecia starting about 1 week after the initial ingestion.
- Treatment of colchicine overdose should begin with gastric lavage and measures to prevent shock. Otherwise, treatment is symptomatic and supportive. No specific antidote is known. Colchicine is not effectively removed by hemodialysis [see Pharmacokinetics (12.3)].

11 DESCRIPTION

Colchicine is an alkaloid obtained from the plant colchicum autumnale.

The chemical name for colchicine is (S) -N-(5,6,7,9- tetrahydro-1,2,3,10-tetramethoxy-9 oxobenzol[a]heptalen-7-yl) acetamide. The structural formula is represented below:

Colchicine consists of pale yellow scales or powder; it darkens on exposure to light. Colchicine is soluble in water, freely soluble in alcohol, and slightly soluble in ether.

Colchicine capsules are supplied for oral administration. Each capsule contains 0.6 mg colchicine, USP and the following inactive ingredients: colloidal silicon dioxide, lactose anhydrous, magnesium stearate, microcrystalline cellulose, and sodium starch glycolate. The capsule shell contains gelatin, purified water, titanium dioxide, erythrosine, Brilliant Blue FCF, and may contain D&C Red No. 28, FD&C Red No. 40 and Quinoline Yellow.

12 CLINICAL PHARMACOLOGY

12.1 Mechanism of Action

Colchicine’s effectiveness as a treatment for gout has been postulated to be due to its ability to block neutrophil-mediated inflammatory responses induced by monosodium urate crystals in synovial fluid. Colchicine disrupts the polymerization of β-tubulin into microtubules, thereby preventing the activation, degranulation, and migration of neutrophils to sites of inflammation. Colchicine also interferes with the inflammasome complex found in neutrophils and monocytes that mediates interleukin-1β (IL-1β) activation.

12.3 Pharmacokinetics

Absorption: In healthy adults, colchicine capsules when given orally reached a mean Cmax of 3 ng/mL in 1.3 h (range 0.7 to 2.5 h) after 0.6 mg single dose administration.

Absolute bioavailability is reported to be approximately 45%.

Administration with food has no effect on the rate or extent of colchicine absorption.

Colchicine is not effectively removed by hemodialysis.

Distribution: Colchicine has a mean apparent volume of distribution in healthy young volunteers of approximately 5 to 8 L/kg. Colchicine binding to serum protein is about 39%, primarily to albumin. Colchicine crosses the placenta and distributes into breast milk [see Pregnancy (8.1) and Lactation (8.2)] .

Metabolism: A published in vitro human liver microsome study showed that about 16% of colchicine is metabolized to 2-O-demethylcolchicine and 3-O-demethylcolchicine (2- and 3-DMC, respectively) by CYP3A4. Glucuronidation is also believed to be a metabolic pathway for colchicine.

Excretion: In a published study in healthy volunteers, 40 to 65% of the total absorbed dose of colchicine (1 mg administered orally) was recovered unchanged in urine. Enterohepatic recirculation and biliary excretion are also believed to play a role in colchicine elimination. Colchicine is a substrate of P-gp and P-gp efflux is postulated to play an important role in colchicine disposition. Elimination half-life in humans was found to be 31 h (range 21.7 to 49.9 h).

Special Populations: There is no difference between men and women in the pharmacokinetic disposition of colchicine.

Pediatric Patients: Pharmacokinetics of colchicine was not evaluated in pediatric patients.

Elderly: Pharmacokinetics of colchicine have not been determined in elderly patients. A published report described the pharmacokinetics of 1 mg oral colchicine tablet in four elderly women compared to six young healthy males. The mean age of the four elderly women was 83 years (range 75 to 93), mean weight was 47 kg (38 to 61 kg) and mean creatinine clearance was 46 mL/min (range 25 to 75 mL/min). Mean peak plasma levels and AUC of colchicine were two times higher in elderly subjects compared to young healthy males. It is possible that the higher exposure in the elderly subjects was due to decreased renal function.

Renal impairment: Pharmacokinetics of colchicine in patients with mild and moderate renal impairment is not known. A published report described the disposition of colchicine (1 mg) in young adult men and women patients who had end-stage renal disease requiring dialysis compared to patients with normal renal function. Patients with end-stage renal disease had 75% lower colchicine clearance (0.17 vs. 0.73 L/hr/kg) and prolonged plasma elimination half-life (18.8 hrs vs. 4.4 hrs) as compared to subjects with normal renal function [see Renal Impairment (8.6)] .

Hepatic impairment: Published reports on the pharmacokinetics of intravenous colchicine in patients with severe chronic liver disease, as well as those with alcoholic or primary biliary cirrhosis, and normal renal function suggest wide inter-patient variability. In some subjects with mild to moderate cirrhosis, the clearance of colchicine is significantly reduced and plasma half-life prolonged compared to healthy subjects. In subjects with primary biliary cirrhosis, no consistent trends were noted [see Hepatic Impairment (8.7)] . No pharmacokinetic data are available for patients with severe hepatic impairment (Child-Pugh C).

Drug Interactions: Pharmacokinetic studies evaluating changes in systemic levels of colchicine when co-administered with CYP3A4 inhibitors in healthy volunteers have been conducted with colchicine capsules. While voriconazole 200 mg BID for 5 days (considered a strong CYP3A4 inhibitor) and cimetidine 800 mg BID for 5 days (considered a weak CYP3A4 inhibitor) did not cause any changes in colchicine systemic levels, fluconazole 200 mg QD for 4 days with a 400 mg loading dose (considered a moderate CYP3A4 inhibitor) increased colchicine AUC by 40%. As voriconazole, cimetidine, and fluconazole are known as CYP3A4 inhibitors that do not inhibit P-gp, these studies show that CYP3A4 inhibition by itself may not lead to clinically significant increases in colchicine systemic levels in humans, and P-gp inhibition in addition to CYP3A4 inhibition may be necessary for clinically meaningful interactions of colchicine. However, based on published case reports that indicate the presence of colchicine toxicity when colchicine is co-administered with strong to moderate CYP3A4 inhibitors such as clarithromycin, erythromycin, grapefruit juice, etc., as well as the 40% increase in systemic levels of colchicine observed with concomitantly administered fluconazole (a moderate CYP3A4 inhibitor that is not known to inhibit P-gp) in a drug-drug interaction study, the drug-drug interaction potential of colchicine with strong or moderate CYP3A4 inhibitors that do not inhibit P-gp cannot be ruled out completely.

Co-administration of colchicine capsules with propafenone (a P-gp inhibitor) at 225 mg BID for 5 days, in a pharmacokinetic study in healthy volunteers, did not cause any changes in systemic levels of colchicine. This indicates that propafenone can be administered with colchicine capsules without any dose adjustment. However, these results should not be extrapolated to other P-gp inhibitors as colchicine is known to be a substrate for P‑gp and case reports of colchicine toxicity associated with the co-administration of P-gp inhibitors such as cyclosporine have been published.

13 NONCLINICAL TOXICOLOGY

13.1 Carcinogenesis, Mutagenesis, Impairment of Fertility

Carcinogenesis
Carcinogenicity studies of colchicine have not been conducted. Due to the potential for colchicine to produce aneuploid cells (cells with an unequal number of chromosomes), colchicine presents a theoretical increased risk of malignancy.

Mutagenesis
Published studies demonstrated that colchicine was negative for mutagenicity in the bacterial reverse mutation assay. However, in vitrochromosomal aberration assays demonstrated the formation of micronuclei following colchicine treatment. Because published studies demonstrated that colchicine induces aneuploidy through the process of mitotic nondisjunction without structural DNA changes, colchicine is not considered clastogenic, although micronuclei are formed.

Impairment of Fertility
There were no studies of the effects of colchicine capsules on fertility. However, published nonclinical studies have demonstrated that colchicine-induced disruption of microtubule formation affects meiosis and mitosis. Published reproductive studies with colchicine reported abnormal sperm morphology and reduced sperm counts in males, and interference with sperm penetration, second meiotic division, and normal cleavage in females.

Case reports and epidemiology studies in human male subjects on colchicine therapy indicate that infertility from colchicine is rare. A case report indicated that azoospermia was reversed when therapy was stopped. Case reports and epidemiology studies in female subjects on colchicine therapy have not established a clear relationship between colchicine use and female infertility.

14 CLINICAL STUDIES

The evidence for the efficacy of colchicine in patients with chronic gout is derived from the published literature. Two randomized clinical trials assessed the efficacy of colchicine 0.6 mg twice a day for the prophylaxis of gout flares in patients with gout initiating treatment with urate lowering therapy. In both trials, treatment with colchicine decreased the frequency of gout flares.

16 HOW SUPPLIED/STORAGE AND HANDLING

16.1 How Supplied

Colchicine capsules, 0.6 mg are No. 4 Dark Blue/Light Blue Hard Gelatin Capsules printed “West-ward 118” in white ink.

Unit dose packages of 30 (5 x 6) NDC 60687-358-25

16.2 Storage

Store at 20°C to 25°C (68°F to 77°F). [See USP Controlled Room Temperature].
Protect from light and moisture.

FOR YOUR PROTECTION: Do not use if blister is torn or broken.

17 PATIENT COUNSELING INFORMATION

Advise the patient to read the FDA-approved patient labeling (Medication Guide).

Dosing Instructions: If a dose of colchicine capsules is missed, advise the patient to take the dose as soon as possible and then return to the normal dosing schedule. However, if a dose is skipped, the patient should not double the next dose.

Fatal Overdose: Advise the patient that fatal overdoses, both accidental and intentional, have been reported in adults and children who have ingested colchicine. Colchicine capsules should be kept out of the reach of children.

Blood Dyscrasias: Advise patients that bone marrow depression with agranulocytosis, aplastic anemia, and thrombocytopenia may occur with colchicine capsules.

Drug and Food Interactions: Advise patients that many drugs or other substances may interact with colchicine capsules and some interactions could be fatal. Therefore, patients should report to their healthcare provider all of the current medications they are taking, and check with their healthcare provider before starting any new medications, including short-term medications such as antibiotics. Patients should also be advised to report the use of non-prescription medication or herbal products. Grapefruit and grapefruit juice may also interact and should not be consumed during treatment with colchicine capsules.

Neuromuscular Toxicity: Advise patients that muscle pain or weakness, tingling or numbness in fingers or toes may occur with colchicine capsules alone or when it is used with certain other drugs. Patients developing any of these signs or symptoms must discontinue colchicine capsules and seek medical evaluation immediately.

Infertility: Advise males of reproductive potential that colchicine capsules may rarely and transiently impair fertility [see Use in Specific Populations (8.3)].

PACKAGING INFORMATION

American Health Packaging unit dose blisters (see How Supplied section) contain drug product from Hikma Pharmaceuticals USA Inc. as follows:
(0.6 mg / 30 UD) NDC 60687-358-25 packaged from NDC 0143-3018

Distributed by:
American Health Packaging
Columbus, OH 43217

8435825/0425F

Medication Guide

8435825/0425F

Colchicine (kol’ chi seen) Capsules

What is the most important information I should know about colchicine capsules?
Colchicine capsules can cause serious side effects or death if levels of colchicine are too high in your body.

- Taking certain medicines with colchicine capsules can cause your level of colchicine to be too high, especially if you have kidney or liver problems.
- Tell your healthcare provider about all your medical conditions, including if you have kidney or liver problems. Your dose of colchicine capsules may need to be changed.
- Even medicines that you take for a short period of time, such as antibiotics, can interact with colchicine capsules and cause serious side effects or death.

What are colchicine capsules?
Colchicine capsules are a prescription medication used to prevent gout flares in adults.

It is not known if colchicine capsules are safe and effective for the treatment of:

- acute gout flares

Colchicine capsules are not a pain medicine and it should not be taken to treat pain related to other conditions unless specifically for those conditions.

It is not known if colchicine capsules are safe and effective in children.

Who should not take colchicine capsules?
Do not take colchicine capsules if you have liver and kidney problems and you take certain other medicines. Serious side effects, including death, have been reported in these people even when taken as directed. See “What is the most important information I should know about colchicine capsules?”

What should I tell my healthcare provider before taking colchicine capsules?
Before you take colchicine capsules, tell your healthcare provider:

- about all of your medical conditions
- if you have kidney or liver problems
- if you are pregnant or plan to become pregnant. It is not known if colchicine capsules can harm your unborn baby. Talk to your healthcare provider if you are pregnant or plan to become pregnant.
- if you are breastfeeding or plan to breastfeed. Colchicine can pass into your breast milk and may harm your baby. Talk to your healthcare provider about the best way to feed your baby if you take colchicine capsules.
- if you are a male with a female partner who can become pregnant. Receiving treatment with colchicine capsules maybe related to infertility in some men that is reversible whentreatment is stopped.

Tell your healthcare provider about all the medicines you take, including prescription, over-the-counter medicines, vitamins, or herbal supplements.

- Using colchicine capsules with certain other medicines can affect each other causing serious side effects and/or death.
- Do not take colchicine capsules with other medicines unless your healthcare provider tells you to.
- Know the medicines you take. Keep a list of your medicines with you to show your healthcare provider and pharmacist each time you get a new medicine.
- Especially tell your healthcare provider if you take:
  - medicines that may affect how your liver works (CYP3A4 inhibitors)
  - cyclosporine (Neoral, Gengraf, Sandimmune)
  - cholesterol lowering medicines
  - antibiotics

Ask your healthcare provider or pharmacist if you are not sure if you take any of the medicines listed above. This is not a complete list of all the medicines that can affect colchicine capsules.

How should I take colchicine capsules?

- Take colchicine capsules exactly as your healthcare provider tells you to take it.
- Colchicine capsules can be taken with or without food.
- If you take too much colchicine capsules, call your healthcare provider or go to the nearest hospital emergency room right away.
- Do not stop taking colchicine capsules unless your healthcare provider tells you to.
- If you miss a dose of colchicine capsules, take it as soon as you remember. If it is almost time for your next dose, skip the missed dose. Take the next dose at your regular time. Do not take 2 doses at the same time.
- If you have a gout flare while taking colchicine capsules, tell your healthcare provider.

What should I avoid while taking colchicine capsules?

- Avoid eating grapefruit or drinking grapefruit juice while taking colchicine capsules. It can increase your chances of getting serious side effects.

What are the possible side effects of colchicine capsules?
Colchicine capsules can cause serious side effects or death.

See “What is the most important information I should know about colchicine capsules?”
Get medical help right away, if you have:

- unusual bleeding or bruising
- increased infections
- weakness or fatigue
- muscle weakness or pain
- numbness or tingling in your fingers or toes
- pale or gray color to your lips, tongue, or palms of your hands
- severe diarrhea or vomiting

The most common side effects of colchicine capsules include abdominal pain, diarrhea, nausea, and vomiting.

Tell your healthcare provider if you have any side effect that bothers you or that does not go away.

These are not all of the possible side effects of colchicine capsules. For more information ask your healthcare provider or pharmacist.

Call your doctor for medical advice about side effects. You may report side effects to FDA at 1-800-FDA-1088.

How should I store colchicine capsules?

- Store colchicine capsules at room temperature between 68°F to 77°F (20°C to 25°C).
- Keep colchicine capsules out of the light and away from moisture.

Keep colchicine capsules and all medicines out of the reach of children.

General information about the safe and effective use of colchicine capsules.
Medicines are sometimes prescribed for purposes other than those listed in a Medication Guide. Do not take colchicine capsules for a condition for which it was not prescribed. Do not give colchicine capsules to other people, even if they have the same symptoms that you have. It may harm them.

This Medication Guide summarizes the most important information about colchicine capsules. If you would like more information, talk to your pharmacist or healthcare provider for information about colchicine capsules that is written for health professionals.

For more information about the drug product, go to www.hikma.com or call 1-800-962-8364.

For more information about the packaging or labeling, call American Health Packaging at 1‐800‐707‐4621.

What are the ingredients in colchicine capsules?
Active Ingredient: Colchicine, USP
Inactive Ingredients:colloidal silicon dioxide, lactose anhydrous, magnesium stearate, microcrystalline cellulose and sodium starch glycolate. The capsule shell contains gelatin, purified water, titanium dioxide, erythrosine, Brilliant Blue FCF, and may contain D&C Red No. 28, FD&C Red No. 40 and Quinoline Yellow.

This Medication Guide has been approved by the U.S. Food and Drug Administration.

Distributed by:
American Health Packaging
Columbus, OH 43217

8435825/0425F

Package/Label Display Panel – Carton – 0.6 mg

NDC 60687- 358-25

Colchicine
Capsules

0.6 mg

30 Capsules (5 x 6) Rx Only

PHARMACIST: Dispense with Medication Guide to
each patient.

Each Capsule Contains:
Colchicine, USP............................................................0.6 mg

Usual Adult Dosage: See package full prescribing information.

Store at 20° to 25°C (68° to 77°F); excursions permitted
between 15° to 30°C (59° to 86°F) [see USP Controlled
Room Temperature].
PROTECT FROM LIGHT AND MOISTURE.

FOR YOUR PROTECTION: Do not use if blister is torn
or broken.

The drug product contained in this package is from
NDC # 0143-3018, Hikma Pharmaceuticals USA Inc.

Distributed by: American Health Packaging, Columbus,
Ohio 43217

735825
0435825/0324

Package/Label Display Panel – Blister – 0.6 mg

Colchicine
Capsule

0.6 mg